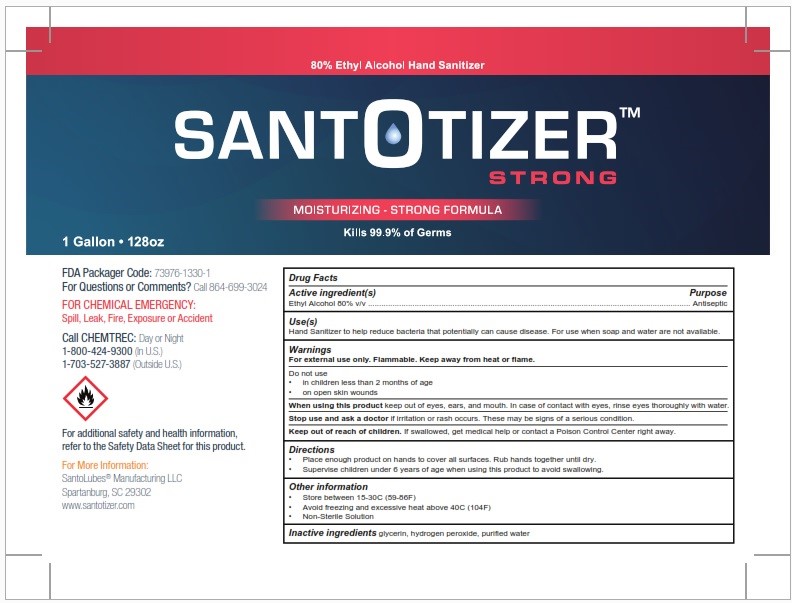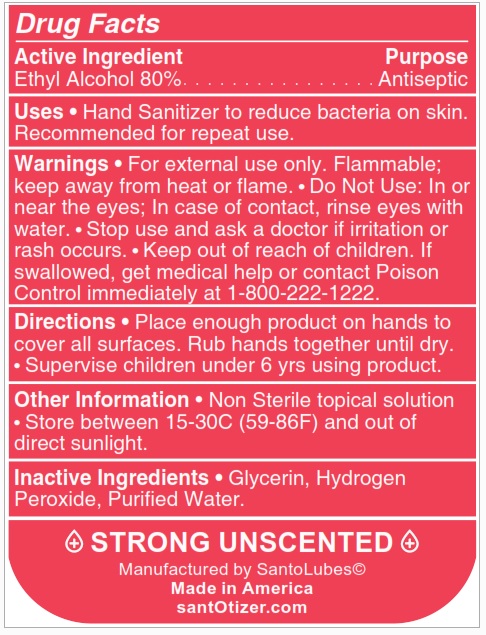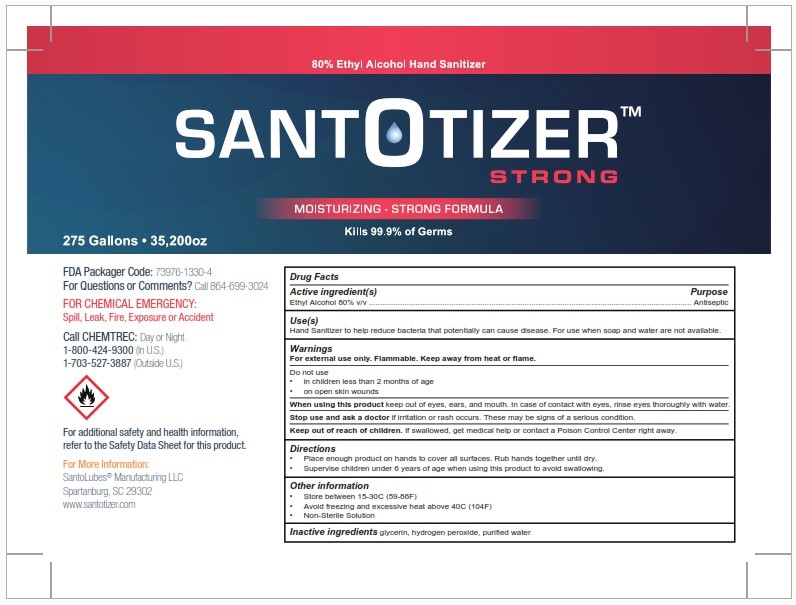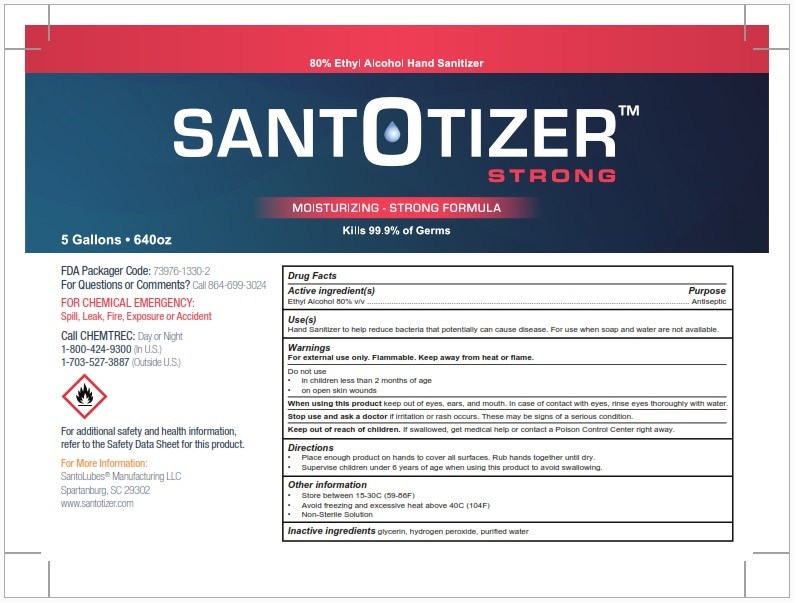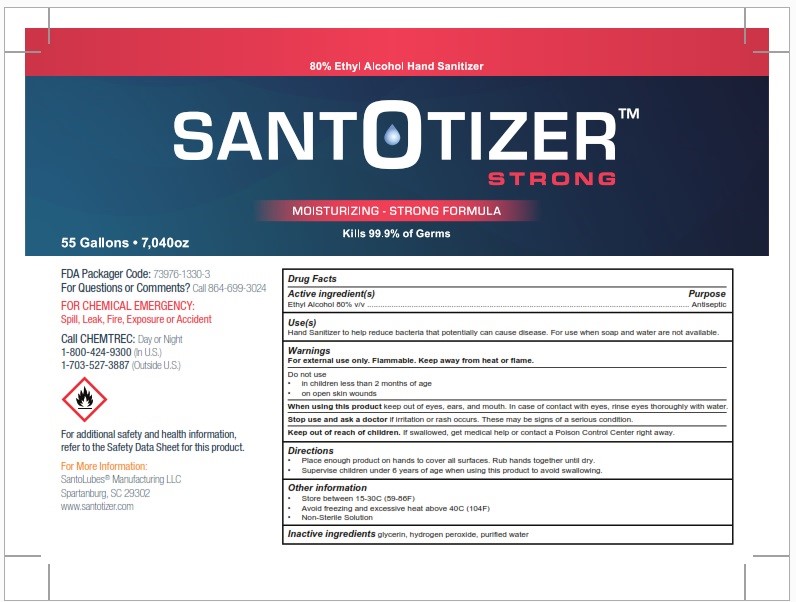 DRUG LABEL: Santotizer
NDC: 73976-1330 | Form: LIQUID
Manufacturer: Santolubes LLC
Category: otc | Type: HUMAN OTC DRUG LABEL
Date: 20210429

ACTIVE INGREDIENTS: ALCOHOL 80 L/100 L
INACTIVE INGREDIENTS: HYDROGEN PEROXIDE 0.125 L/100 L; WATER 18.4 L/100 L; GLYCERIN 1.45 L/100 L

Directions

Place enough product on hands to cover all surfaces. Rub hands together until dry.
Supervise children under 6 years of age when using this product to avoid swallowing.

Warnings

For external use only. Flammable. Keep away from heat or flame.

Inactive ingredients glycerin, hydrogen peroxide, purified water

INDICATIONS AND USAGE

Use[s]

Hand Sanitizer to help reduce bacteria that potentially can cause disease. For use when soap and water are not available.

Keep out of reach of children. If swallowed, get medical help or contact a Poison Control Center right away.

Purpose

Antiseptic

changed label

PACKAGE LABEL

3,600ml NDC 73976-1330-1

18,000ml NDC 73976-1330-2

200,000ml NDC 73976-1330-3

1,022,000ml NDC 73976-1330-4